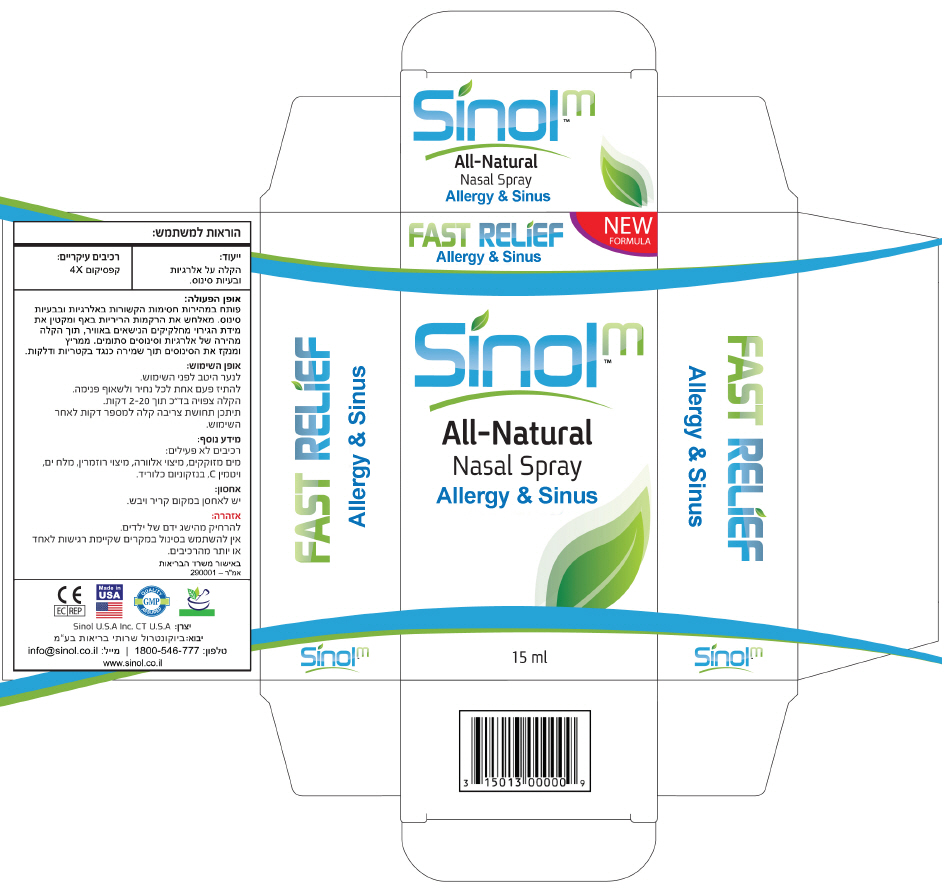 DRUG LABEL: SinolM Fast Allergy and Sinus Relief 

NDC: 15013-000 | Form: SPRAY
Manufacturer: Sinol USA, Inc.
Category: otc | Type: HUMAN OTC DRUG LABEL
Date: 20250129

ACTIVE INGREDIENTS: CAPSICUM 4 [hp_X]/0.263 mL
INACTIVE INGREDIENTS: WATER; SILVER; ALOE; EUCALYPTOL; ROSEMARY; SEA SALT; ASCORBIC ACID

SinolM™ Fast Allergy and Sinus Relief
All-Natural Nasal Spray

PRINCIPAL DISPLAY PANEL - 15 ml Bottle Box

FAST RELIEF
Allergy & Sinus

NEW
FORMULA

Sinolm™
All-Natural
Nasal Spray
Allergy & Sinus

15 ml